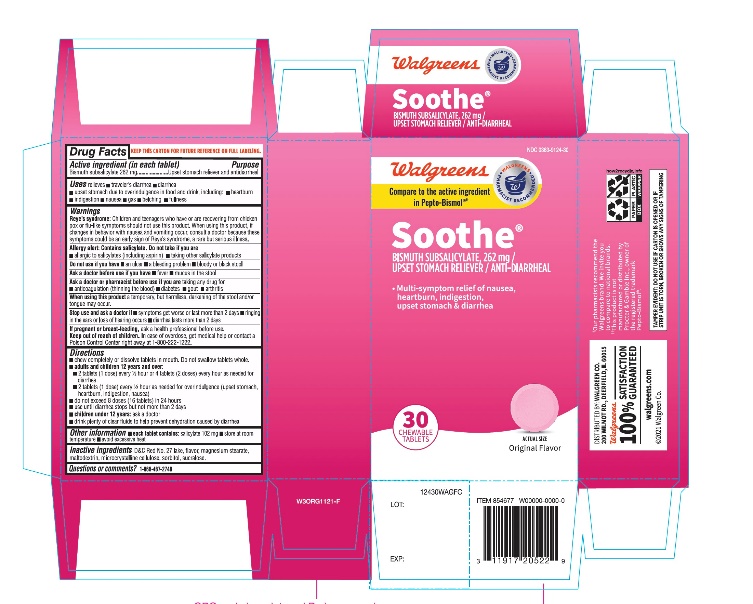 DRUG LABEL: Walgreen
NDC: 0363-9124 | Form: TABLET, CHEWABLE
Manufacturer: WALGREEN COMPANY
Category: otc | Type: HUMAN OTC DRUG LABEL
Date: 20251125

ACTIVE INGREDIENTS: BISMUTH SUBSALICYLATE 262 mg/1 1
INACTIVE INGREDIENTS: MAGNESIUM STEARATE; MALTODEXTRIN; MICROCRYSTALLINE CELLULOSE; D&C RED NO. 27; SORBITOL; SUCRALOSE

Walgreen Soothe Bismuth Subsalicylate Chewable Tablets

Drug Facts

Active ingredient (in each chewable tablet)

Bismuth subsalicylate 262 mg

Purpose

Anti-diarrheal / upset stomach reliever

Uses

relieves:

- travelers’ diarrhea
- diarrhea
- upset stomach due to overindulgence in food and drink, including:
- heartburn
- indigestion
- nausea
- gas
- belching
- fullness

Warnings

Reye's syndrome:Children and teenagers who have or are recovering from chicken pox or flu-like symptoms should not use this product. When using this product, if changes in behavior with nausea and vomiting occur, consult a doctor because these symptoms could be an early sign of Reye's syndrome, a rare but serious illness.

Allergy alert:Contains salicylates. Do not take if you are:

- allergic to salicylates (including aspirin)
- taking other salicylate products

Do not use if you have

- an ulcer
- a bleeding problem
- bloody or black stool

Ask a doctor before use if you have

- fever
- mucus in the stool

Ask a doctor or pharmacist before use if you aretaking any drug for

- anticoagulation (thinning the blood)
- diabetes
- gout
- arthritis

WHEN USING

When using this producta temporary, but harmless, darkening of the stool and/or tongue may occur.

Stop use and ask a doctor if

- symptoms get worse or last more than 2 days
- ringing in the ears or loss of hearing occurs
- diarrhea lasts more than 2 days

PREGNANCY OR BREAST FEEDING

If pregnant or breast-feeding,ask a health professional before use.

Keep out of reach of children.In case of overdose, get medical help or contact a Poison Control Center right away at 1-800-222-1222.

Directions

- chew or dissolve tablet in mouth
- adults and children 12 years and over:2 tablets every 1/2 to 1 hour as needed.
  Do not exceed 8 doses (16 tablets) in 24 hours.
- use until diarrhea stops, but not more than 2 days
- drink plenty of clear fluids to help prevent dehydration caused by diarrhea
- children under 12 years:ask a doctor

Other information

- each tablet contains: salicylate 102 mg
- store at room temperature
- avoid excessive heat

Inactive ingredients

flavor, magnesium stearate, maltodextrin, microcrystalline, cellulose, red #27 (Al-lake), sorbitol, sucralose.

Questions or comments?

Call 1- 866-467-2748

TAMPER EVIDENT: DO NOT USE IF CARTON IS OPENED OR IF BLISTER UNIT IS TORN, BROKEN OR SHOWS ANY SIGNS OF TEMPERING.

*Walgreen Pharmacist Recommended Walgreens Pharmacist Survey.

††This product is not manufactured or distributed by Procter & Gamble, owner of the registered trademark Pepto-Bismol®

DISTRIBUTED BY: WALGREEN CO.

200 WILMOT RD., DEERFIELD, IL 60015

100% SATISFACTION GUARANTEED

walgreens.com© 2018 Walgreen Co.

PACKAGE LABEL

NDC 0363-9124-30

Walgreens

Soothe®

BISMUTH SUBSALICYLATE, 262 MG

UPSET STOMACH RELIEVER / ANTI-DIARRHEAL

30 CHEWABLE TABLETS

Multi-symptom relief of nausea, heartburn, indigestion, upset stomach & diarrhea

*Compare to Pepto-Bismol®active ingredient††